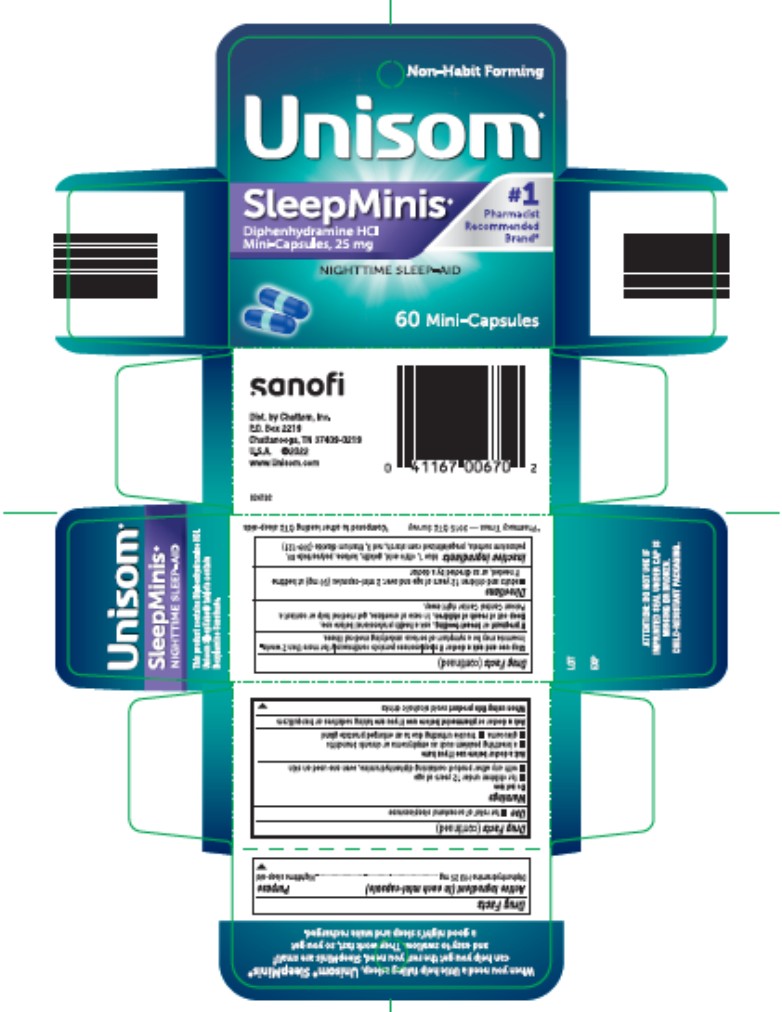 DRUG LABEL: Unisom SleepMinis Nighttime Sleep-Aid
NDC: 41167-0067 | Form: CAPSULE
Manufacturer: Chattem, Inc.
Category: otc | Type: HUMAN OTC DRUG LABEL
Date: 20260114

ACTIVE INGREDIENTS: DIPHENHYDRAMINE HYDROCHLORIDE 25 mg/1 1
INACTIVE INGREDIENTS: FD&C BLUE NO. 1; ANHYDROUS CITRIC ACID; GELATIN; LACTOSE MONOHYDRATE; POLYSORBATE 80; POTASSIUM SORBATE; STARCH, CORN; FD&C RED NO. 3; TITANIUM DIOXIDE

Unisom SleepMinis Nighttime Sleep-Aid

Drug Facts

Active ingredient

(in each mini-capsule)

Diphenhydramine HCI 25 mg

Purpose

Nighttime sleep-aid

Use

- for relief of occasional sleeplessness

Warnings

Do not use

- for children under 12 years of age
- with any other product containing diphenhydramine, even one used on skin

Ask a doctor before use if you have

- a breathing problem such as emphysema or chronic bronchitis
- glaucoma
- trouble urinating due to an enlarged prostate gland

Ask a doctor or pharmacist before use if you are

taking sedatives or tranquilizers

When using this product

- avoid alcoholic drinks

Stop use and ask a doctor if

- sleeplessness persist continuously for more than 2 weeks. Insomnia may be a symptom of serious underlying medical illness.

If pregnant or breast-feeding,

ask a health professional before use.

Keep out of reach of children.

In case of overdose, get medical help or contact a Poison Control Center right away.

Directions

- adults and children 12 years of age and over: 2 mini-capsules (50 mg) at bedtime if needed, or as directed by a doctor

Inactive ingredients

blue 1, citric acid, gelatin, lactose, polysorbate 80, potassium sorbate, pregelatinized corn starch, red 3, titanium dioxide (309-121)

PRINCIPAL DISPLAY PANEL

Unisom
#1 Pharmacist Recommended Ingredient*
SleepMinis
Diphenhydramine HCI
Mini-Capsules, 25 mg
NIGHTTIME SLEEP-AID
60 Mini-Capsules